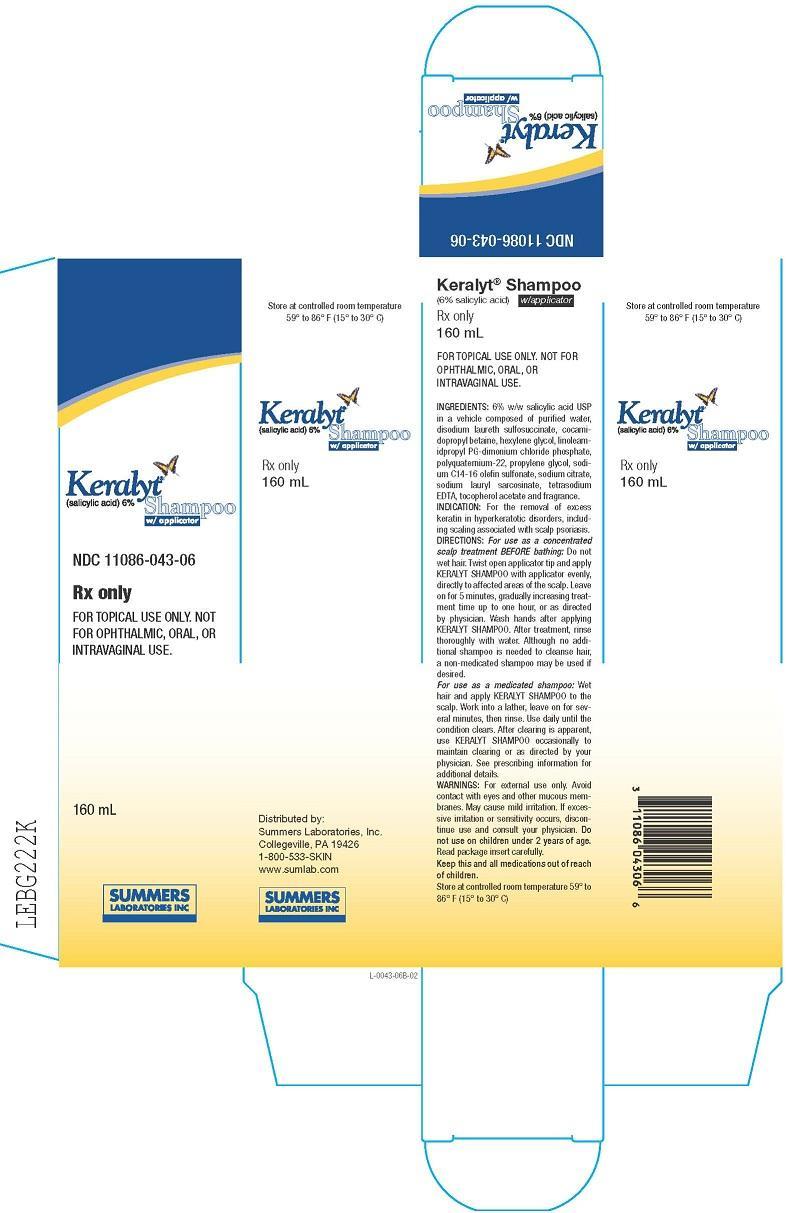 DRUG LABEL: Keralyt
NDC: 11086-043 | Form: SHAMPOO
Manufacturer: Summers Laboratories Inc
Category: prescription | Type: HUMAN PRESCRIPTION DRUG LABEL
Date: 20231009

ACTIVE INGREDIENTS: SALICYLIC ACID 6 g/92.6 mL

SUMMERS LABS (as PLD) - Keralyt Shampoo (11086-043)

DESCRIPTION

DESCRIPTION:KERALYT® shampoo contains 6% w/w salicylic acid USP in a vehicle composed of purified water, ammonium lauryl sulfosuccinate, cocamidopropyl betaine, hexylene glycol, linoleamidopropyl PG-dimonium chloride phosphate, polyquaternium-22, propylene glycol, sodium C14-16 olefin sulfonate, sodium citrate, sodium lauroyl sarcosinate, tetrasodium EDTA, tocopherol acetate and fragrance.

Salicylic acid is the 2 hydroxy derivative of benzoic acid

CLINICAL PHARMACOLOGY

CLINICAL PHARMACOLOGY:Salicylic acid has been shown to produce desquamation of the horny layer of skin while not affecting qualitative or quantitative changes in structure of the viable epidermis. ¹, ²The mechanism of action has been attributed to a dissolution of intercellular cement substance. ³In a study of the percutaneous absorption of salicylic acid in four patients with extensive active psoriasis, Taylor and Halprin ⁴showed that peak serum salicylate levels never exceeded 5 mg/100 ml even though more than 60% of the applied salicylic acid was absorbed. Systemic toxic reactions are usually associated with much higher serum levels (30 to 40 mg/100 ml). Peak serum levels occurred within 5 hours of the topical application under occlusion. The sites were occluded for 10 hours over the entire body surface below the neck. Since salicylates are distributed in the extracellular space, patients with a contracted extracellular space due to dehydration or diuretics have higher salicylate levels than those with a normal extracellular space. ⁵(See PRECAUTIONS).

The major metabolites identified in the urine after topical administration are salicyluric acid (52%), salicylate glucuronides (42%), and free salicylic acid (6%). ⁴The urinary metabolites after percutaneous absorption differ from those after oral salicylate administration; those derived from percutaneous absorption contain more glucuronides and less salicyluric and salicylic acid. Almost 95% of a single dose of salicylate is excreted within 24 hours of its entrance into the extracellular space. ⁵

Fifty to eighty percent of salicylate is protein bound to albumin. Salicylates compete with the binding of several drugs and can modify the action of these drugs. By similar competitive mechanisms other drugs can influence the serum levels of salicylate. ⁵(See PRECAUTIONS).

INDICATIONS AND USAGE- For the removal of excess keratin in hyperkeratotic disorders, including scaling associated with scalp psoriasis or thickened skin of palms and soles, corns and calluses.

CONTRAINDICATIONS

CONTRAINDICATIONS:KERALYT SHAMPOO should not be used in any patient known to be sensitive to salicylic acid or any other listed ingredient. KERALYT SHAMPOO should not be used in children under 2 years of age.

WARNINGS

WARNINGS:Prolonged use over large areas, especially in children and those patients with significant renal or hepatic impairment, could result in salicylism. Concomitant use of other drugs which may contribute to elevated serum salicylate levels should be avoided where the potential for toxicity is present. In children under 12 years of age and those patients with renal or hepatic impairment, the area to be treated should be limited and the patient monitored closely for signs of salicylate toxicity: nausea, vomiting, dizziness, loss of hearing, tinnitus, lethargy, hyperpnoea, diarrhea, psychic disturbances. In the event of salicylic acid toxicity, the use of KERALYT SHAMPOO should be discontinued. Fluids should be administered to promote urinary excretion. Treat- ment with sodium bicarbonate (oral or intravenous) should be instituted as appropriate.

Considering the potential risk of developing Reye’s Syndrome, salicylate products should not be administered to children or teenagers with varicella or influenza, unless directed by a physician.

PRECAUTIONS

PRECAUTIONS:For external use only. Avoid contact with eyes and other mucous membranes. Mild burning or stinging may occur. Peeling of the skin may increase as the salicylic acid works to loosen excess keratin. If excessive burning, stinging or peeling occurs, discontinue use and consult your physician. Keep this and all medications out of reach of children.

DRUG INTERACTIONS

Drug Interactions.(The following interactions are from a published review ⁵and include reports concerning both oral and topical salicylate administration. The relationship of these interactions to the use of KERALYT SHAMPOO is not known.)

I. Due to the competition of salicylate with other drugs for binding to serum albumin the following drug interactions may occur:

Drug | Description of Interaction
Tolbutamide; Sulfonylureas | Hypoglycemia potentiated
Methotrexate | Decreases tubular reabsorption; clinical toxicity from methotrexate can result
Oral Anticoagulant | Increased bleeding

II. Drugs changing salicylate levels by altering renal tubular reabsorption:

Drug | Description
Corticosteroids | Decreases plasma salicylate level; Tapering doses of steroids may promote salicylism
Ammonium Sulfate | Increases plasma salicylate level

III. Drugs with complicated interactions with salicylates:

Drug | Description
Heparin | Salicylate decreases platelet adhesiveness and interferes with hemostasis in heparin-treated patients
Pyrazinamide | Inhibits pyrazinamide-induced hyperuricemia
Uricosuric Agents | Effect of probenecid, sulfinpyrazone and phenylbutazone inhibited

The following alterations of laboratory tests have been reported during salicylate therapy ⁶:

Laboratory Tests | Effect of Salicylates
Thyroid Function | Decreased PBI; increased T3uptake
Urinary Sugar | False negative with glucose oxidase; false positive with Clinitest with high-dose salicylate therapy (2-5 g qd)
5 Hydroxyindole acetic acid | False negative with fluorometric test
Acetone, Ketone Bodies | False positive FeCl3in Gerhardt reaction; red color persists with boiling
17-OH corticosteroids | False reduced values with >4.8 g qd salicylate
Vanilmandelic Acid | False reduced values
Uric Acid | May increase or decrease depending on dose
Prothrombin | Decreased levels; slightly increased prothrombin time

PREGNANCY

Pregnancy (Category C):Salicylic acid has been shown to be teratogenic in rats and monkeys. It is difficult to extrapolate from oral doses of acetyl salicylic acid used in these studies to topical administration as the oral dose to monkeys may represent 4 times the maximum daily human dose of salicylic acid (as supplied in one bottle, 8 oz. of KERALYT SHAMPOO) when applied topically over a large body surface. There are no adequate and well-controlled studies in pregnant women. KERALYT SHAMPOO should be used during pregnancy only if the potential benefit justifies the risk to the fetus.

NURSING MOTHERS

Nursing Mothers:Because of the potential for serious adverse reactions in nursing infants from the mother’s use of KERALYT SHAMPOO, a decision should be made whether to discontinue nursing or to discontinue the drug, taking into account the importance of the drug to the mother. If used by nursing mothers, it should not be in the chest area in order to avoid accidental exposure to a nursing child.

CARCINOGENESIS AND MUTAGENESIS AND IMPAIRMENT OF FERTILITY

Carcinogenesis, Mutagenesis, Impairment of Fertility:No data are available concerning potential carcinogenic or reproductive effects of KERALYT SHAMPOO. It has been shown to lack mutagenic potential in the Ames Salmonella test.

ADVERSE REACTIONS

ADVERSE REACTIONS:Excessive erythema and scaling conceivably could result from use on open skin lesions.

OVERDOSAGE- See WARNINGS

DOSAGE AND ADMINISTRATION
For use as a concentrated scalp treatment BEFORE bathing: Do not wet hair. Twist open applicator tip and apply KERALYT SHAMPOO w/applicator evenly, directly to affected areas of the scalp. Leave on for 5 minutes, gradually increasing treatment time up to one hour, or as directed by physician. Wash hands after applying KERALYT SHAMPOO w/applicator. After treatment, rinse thoroughly with water. Although no additional shampoo is needed to cleanse hair, a non-medicated shampoo may be used if desired. For use as a medicated shampoo:Wet hair and apply KERALYT SHAMPOO w/applicator to the scalp. Work into a lather, leave on for several minutes, then rinse. Use daily until the condition clears. After clearing is apparent, use KERALYT SHAMPOO w/applicator occasionally to maintain clearing or as directed by your physician.

HOW SUPPLIED

HOW SUPPLIED:160 mL plastic bottles NDC 11086-043-06
Store at controlled room temperature 59° to 86° F (15° to 30° C)

REFERENCES:
1. Davies M, Marks R: Br J Dermatol95: 187-192,1976.
2. Marks R, Davies M, Cattel A: J Invest Dermatol64: 283, 1975.
3. Huber C, Christophers E: Arch Derm Res257: 293-297, 1977.
4. Taylor JR, Halprin KM: Arch Dermatol111: 740-743, 1975.
5. Goldsmith LA: Int J Dermatol18: 32-36.
6. Wilson JG, Ritter EJ, Scott WJ, Fradlein R: Tox Appl Pharmacol41: 67-78, 1977.

SUMMERS
LABORATORIES INC
Manufactured by:
EMS Contract Packaging, Hatfield, PA 19440
Distributed by:
Summers Laboratories, Inc. Collegeville, PA 19426
1-800-533-SKIN (7546) • www.sumlab.com
KERALYT is a trademark of Summers Laboratories, Inc.